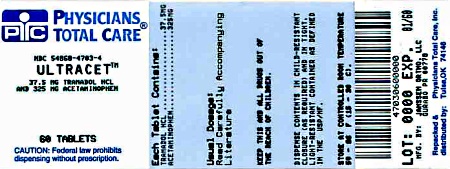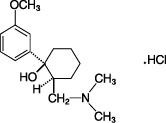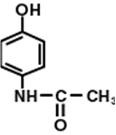 DRUG LABEL: ULTRACET
NDC: 54868-4703 | Form: TABLET, COATED
Manufacturer: Physicians Total Care, Inc.
Category: prescription | Type: HUMAN PRESCRIPTION DRUG LABEL
Date: 20120829

ACTIVE INGREDIENTS: tramadol hydrochloride 37.5 mg/1 1; acetaminophen 325 mg/1 1
INACTIVE INGREDIENTS: powdered cellulose; SODIUM STARCH GLYCOLATE TYPE A POTATO; starch, corn; magnesium stearate; hypromelloses; polyethylene glycols; polysorbate 80; titanium dioxide; FERROSOFERRIC OXIDE; carnauba wax

ULTRACET®
(tramadol hydrochloride/acetaminophen)
Tablets

Full Prescribing Information

HEPATOTOXICITY

ULTRACET® contains tramadol HCl and acetaminophen. Acetaminophen has been associated with cases of acute liver failure, at times resulting in liver transplant and death. Most of the cases of liver injury are associated with the use of acetaminophen at doses that exceed 4,000 milligrams per day, and often involve more than one acetaminophen-containing product (see WARNINGS).

DESCRIPTION

ULTRACET® (tramadol hydrochloride/acetaminophen) Tablets combines two analgesics, tramadol 37.5 mg and acetaminophen 325 mg.

The chemical name for tramadol hydrochloride is (±)cis-2-[(dimethylamino)methyl]-1-(3-methoxyphenyl) cyclohexanol hydrochloride. Its structural formula is:

The molecular weight of tramadol hydrochloride is 299.84. Tramadol hydrochloride is a white, bitter, crystalline, and odorless powder.

The chemical name for acetaminophen is N-acetyl-p-aminophenol. Its structural formula is:

The molecular weight of acetaminophen is 151.17. Acetaminophen is an analgesic and antipyretic agent which occurs as a white, odorless, crystalline powder, possessing a slightly bitter taste.

ULTRACET® tablets contain 37.5 mg tramadol hydrochloride and 325 mg acetaminophen and are light yellow in color. Inactive ingredients in the tablet are powdered cellulose, pregelatinized corn starch, sodium starch glycolate, corn starch, magnesium stearate, hypromellose, polyethylene glycol, polysorbate 80, titanium dioxide, iron oxide, and carnauba wax.

CLINICAL PHARMACOLOGY

The following information is based on studies of tramadol alone or acetaminophen alone, except where otherwise noted:

Pharmacodynamics

ULTRACET® contains tramadol and acetaminophen. Tramadol is a centrally acting synthetic opioid analgesic. Although its mode of action is not completely understood, from animal tests, at least two complementary mechanisms appear applicable: binding of parent and M1 metabolite to µ-opioid receptors and weak inhibition of reuptake of norepinephrine and serotonin.

Opioid activity is due to both low affinity binding of the parent compound and higher affinity binding of the O-demethylated metabolite M1 to µ-opioid receptors. In animal models, M1 is up to 6 times more potent than tramadol in producing analgesia and 200 times more potent in µ-opioid binding. Tramadol-induced analgesia is only partially antagonized by the opiate antagonist naloxone in several animal tests. The relative contribution of both tramadol and M1 to human analgesia is dependent upon the plasma concentrations of each compound (see CLINICAL PHARMACOLOGY, Pharmacokinetics).

Tramadol has been shown to inhibit reuptake of norepinephrine and serotonin in vitro, as have some other opioid analgesics. These mechanisms may contribute independently to the overall analgesic profile of tramadol.

Apart from analgesia, tramadol administration may produce a constellation of symptoms (including dizziness, somnolence, nausea, constipation, sweating, and pruritus) similar to that of other opioids.

Acetaminophen is a non-opiate, non-salicylate analgesic.

Pharmacokinetics

Tramadol is administered as a racemate and both the [-] and [+] forms of both tramadol and M1 are detected in the circulation. The pharmacokinetics of plasma tramadol and acetaminophen following oral administration of one ULTRACET® tablet are shown in Table 1. Tramadol has a slower absorption and longer half-life when compared to acetaminophen.

Table 1: Summary of Mean (±SD) Pharmacokinetic Parameters of the (+)- and (-) Enantiomers of Tramadol and M1 and Acetaminophen Following A Single Oral Dose Of One Tramadol/Acetaminophen Combination Tablet (37.5 mg/325 mg) in Volunteers
Parameter [For acetaminophen, Cmax was measured as µg/mL.] | (+)-Tramadol |  | (-)-Tramadol |  | (+)-M1 |  | (-)-M1 |  | acetaminophen
Cmax (ng/mL) | 64.3 | (9.3) | 55.5 | (8.1) | 10.9 | (5.7) | 12.8 | (4.2) | 4.2 | (0.8)
tmax (h) | 1.8 | (0.6) | 1.8 | (0.7) | 2.1 | (0.7) | 2.2 | (0.7) | 0.9 | (0.7)
CL/F (mL/min) | 588 | (226) | 736 | (244) | - | - | - | - | 365 | (84)
t1/2 (h) | 5.1 | (1.4) | 4.7 | (1.2) | 7.8 | (3.0) | 6.2 | (1.6) | 2.5 | (0.6)

A single-dose pharmacokinetic study of ULTRACET® in volunteers showed no drug interactions between tramadol and acetaminophen. Upon multiple oral dosing to steady state, however, the bioavailability of tramadol and metabolite M1 was lower for the combination tablets compared to tramadol administered alone. The decrease in AUC was 14% for (+)-tramadol, 10.4% for (-)-tramadol, 11.9% for (+)-M1, and 24.2% for (-)-M1. The cause of this reduced bioavailability is not clear. Following single- or multiple-dose administration of ULTRACET®, no significant change in acetaminophen pharmacokinetics was observed when compared to acetaminophen given alone.

Absorption

The absolute bioavailability of tramadol from ULTRACET® tablets has not been determined. Tramadol hydrochloride has a mean absolute bioavailability of approximately 75% following administration of a single 100 mg oral dose of ULTRAM® tablets. The mean peak plasma concentration of racemic tramadol and M1 after administration of two ULTRACET® tablets occurs at approximately two and three hours, respectively, post-dose.

Peak plasma concentrations of acetaminophen occur within one hour and are not affected by co-administration with tramadol. Oral absorption of acetaminophen following administration of ULTRACET® occurs primarily in the small intestine.

Food Effects

When ULTRACET® was administered with food, the time to peak plasma concentration was delayed for approximately 35 minutes for tramadol and almost one hour for acetaminophen. However, peak plasma concentrations, and the extents of absorption, of tramadol and acetaminophen were not affected. The clinical significance of this difference is unknown.

Distribution

The volume of distribution of tramadol was 2.6 and 2.9 L/kg in male and female subjects, respectively, following a 100 mg intravenous dose. The binding of tramadol to human plasma proteins is approximately 20% and binding also appears to be independent of concentration up to 10 µg/mL. Saturation of plasma protein binding occurs only at concentrations outside the clinically relevant range.

Acetaminophen appears to be widely distributed throughout most body tissues except fat. Its apparent volume of distribution is about 0.9 L/kg. A relative small portion (~20%) of acetaminophen is bound to plasma protein.

Metabolism

Following oral administration, tramadol is extensively metabolized by a number of pathways, including CYP2D6 and CYP3A4, as well as by conjugation of parent and metabolites. Approximately 30% of the dose is excreted in the urine as unchanged drug, whereas 60% of the dose is excreted as metabolites. The major metabolic pathways appear to be N- and O- demethylation and glucuronidation or sulfation in the liver. Metabolite M1 (O-desmethyltramadol) is pharmacologically active in animal models. Formation of M1 is dependent on CYP2D6 and as such is subject to inhibition, which may affect the therapeutic response (see PRECAUTIONS, Drug Interactions).

Approximately 7% of the population has reduced activity of the CYP2D6 isoenzyme of cytochrome P450. These individuals are "poor metabolizers" of debrisoquine, dextromethorphan, and tricyclic antidepressants, among other drugs. Based on a population PK analysis of Phase 1 studies in healthy subjects, concentrations of tramadol were approximately 20% higher in "poor metabolizers" versus "extensive metabolizers," while M1 concentrations were 40% lower. In vitro drug interaction studies in human liver microsomes indicate that inhibitors of CYP2D6 such as fluoxetine and its metabolite norfluoxetine, amitriptyline, and quinidine inhibit the metabolism of tramadol to various degrees. The full pharmacological impact of these alterations in terms of either efficacy or safety is unknown. Concomitant use of SEROTONIN re-uptake INHIBITORS and MAO INHIBITORS may enhance the risk of adverse events, including seizure (see WARNINGS) and serotonin syndrome.

Acetaminophen is primarily metabolized in the liver by first-order kinetics and involves three principal separate pathways:

a) conjugation with glucuronide;
b) conjugation with sulfate; and
c) oxidation via the cytochrome, P450-dependent, mixed-function oxidase enzyme pathway to form a reactive intermediate metabolite, which conjugates with glutathione and is then further metabolized to form cysteine and mercapturic acid conjugates. The principal cytochrome P450 isoenzyme involved appears to be CYP2E1, with CYP1A2 and CYP3A4 as additional pathways.

In adults, the majority of acetaminophen is conjugated with glucuronic acid and, to a lesser extent, with sulfate. These glucuronide-, sulfate-, and glutathione-derived metabolites lack biologic activity. In premature infants, newborns, and young infants, the sulfate conjugate predominates.

Elimination

Tramadol is eliminated primarily through metabolism by the liver and the metabolites are eliminated primarily by the kidneys. The plasma elimination half-lives of racemic tramadol and M1 are approximately 5–6 and 7 hours, respectively, after administration of ULTRACET®. The apparent plasma elimination half-life of racemic tramadol increased to 7–9 hours upon multiple dosing of ULTRACET®.

The half-life of acetaminophen is about 2 to 3 hours in adults. It is somewhat shorter in children and somewhat longer in neonates and in cirrhotic patients. Acetaminophen is eliminated from the body primarily by formation of glucuronide and sulfate conjugates in a dose-dependent manner. Less than 9% of acetaminophen is excreted unchanged in the urine.

Special Populations

Renal

The pharmacokinetics of ULTRACET® in patients with renal impairment has not been studied. Based on studies using tramadol alone, excretion of tramadol and metabolite M1 is reduced in patients with creatinine clearance of less than 30 mL/min. Adjustment of dosing regimen in this patient population is recommended (see DOSAGE AND ADMINISTRATION). The total amount of tramadol and M1 removed during a 4-hour dialysis period is less than 7% of the administered dose based on studies using tramadol alone.

Hepatic

The pharmacokinetics and tolerability of ULTRACET® in patients with impaired hepatic function have not been studied. Since tramadol and acetaminophen are both extensively metabolized by the liver, the use of ULTRACET® in patients with hepatic impairment is not recommended (see PRECAUTIONS and DOSAGE AND ADMINISTRATION).

Geriatric

A population pharmacokinetic analysis of data obtained from a clinical trial in patients with chronic pain treated with ULTRACET®, which included 55 patients between 65 and 75 years of age and 19 patients over 75 years of age, showed no significant changes in the pharmacokinetics of tramadol and acetaminophen in elderly patients with normal renal and hepatic function (see PRECAUTIONS, Geriatric Use).

Gender

Tramadol clearance was 20% higher in female subjects compared to males on four phase I studies of ULTRACET® in 50 male and 34 female healthy subjects. The clinical significance of this difference is unknown.

Pediatric

The pharmacokinetics of ULTRACET® tablets has not been studied in pediatric patients below 16 years of age.

CLINICAL STUDIES

Single-Dose Studies for Treatment of Acute Pain

In pivotal single-dose studies in acute pain, two tablets of ULTRACET® administered to patients with pain following oral surgical procedures provided greater relief than placebo or either of the individual components given at the same dose. The onset of pain relief after ULTRACET® was faster than tramadol alone. Onset of analgesia occurred in less than one hour. The duration of pain relief after ULTRACET® was longer than acetaminophen alone. Analgesia was generally comparable to that of the comparator, ibuprofen.

INDICATIONS AND USAGE

ULTRACET® is indicated for the short-term (five days or less) management of acute pain.

CONTRAINDICATIONS

ULTRACET® should not be administered to patients who have previously demonstrated hypersensitivity to tramadol, acetaminophen, any other component of this product, or opioids. ULTRACET® is contraindicated in any situation where opioids are contraindicated, including acute intoxication with any of the following: alcohol, hypnotics, narcotics, centrally acting analgesics, opioids, or psychotropic drugs. ULTRACET® may worsen central nervous system and respiratory depression in these patients.

WARNINGS

Hepatotoxicity

ULTRACET® contains tramadol HCl and acetaminophen. Acetaminophen has been associated with cases of acute liver failure, at times resulting in liver transplant and death. Most of the cases of liver injury are associated with the use of acetaminophen at doses that exceed 4,000 milligrams per day, and often involve more than one acetaminophen-containing product. The excessive intake of acetaminophen may be intentional to cause self-harm or unintentional as patients attempt to obtain more pain relief or unknowingly take other acetaminophen-containing products (see Boxed Warning).

The risk of acute liver failure is higher in individuals with underlying liver disease and in individuals who ingest alcohol while taking acetaminophen.

Instruct patients to look for acetaminophen or APAP on package labels and not to use more than one product that contains acetaminophen. Instruct patients to seek medical attention immediately upon ingestion of more than 4,000 milligrams of acetaminophen per day, even if they feel well.

Seizure Risk

Seizures have been reported in patients receiving tramadol within the recommended dosage range. Spontaneous post-marketing reports indicate that seizure risk is increased with doses of tramadol above the recommended range. Concomitant use of tramadol increases the seizure risk in patients taking:

- Selective serotonin reuptake inhibitors (SSRI antidepressants or anorectics),
- Tricyclic antidepressants (TCAs), and other tricyclic compounds (e.g., cyclobenzaprine, promethazine, etc.), or
- Other opioids.

Administration of tramadol may enhance the seizure risk in patients taking:

- MAO inhibitors (see also WARNINGS, Use with MAO Inhibitors and Serotonin Re-uptake Inhibitors),
- Neuroleptics, or
- Other drugs that reduce the seizure threshold.

Risk of convulsions may also increase in patients with epilepsy, those with a history of seizures, or in patients with a recognized risk for seizure (such as head trauma, metabolic disorders, alcohol and drug withdrawal, or CNS infections). In tramadol overdose, naloxone administration may increase the risk of seizure.

Suicide Risk

- Do not prescribe ULTRACET® for patients who are suicidal or addiction-prone.
- Prescribe ULTRACET® with caution for patients taking tranquilizers or antidepressant drugs and patients who use alcohol in excess and who suffer from emotional disturbance or depression.

The judicious prescribing of tramadol is essential to the safe use of this drug. With patients who are depressed or suicidal, consideration should be given to the use of non-narcotic analgesics.

Tramadol-related deaths have occurred in patients with previous histories of emotional disturbances or suicidal ideation or attempts as well as histories of misuse of tranquilizers, alcohol, and other CNS-active drugs (see WARNINGS, Risk of Overdosage).

Serotonin Syndrome Risk

The development of a potentially life-threatening serotonin syndrome may occur with the use of tramadol products, including ULTRACET®, particularly with concomitant use of serotonergic drugs such as SSRIs, SNRIs, TCAs, MAOIs, and triptans, with drugs which impair metabolism of serotonin (including MAOIs), and with drugs which impair metabolism of tramadol (CYP2D6 and CYP3A4 inhibitors). This may occur within the recommended dose (see CLINICAL PHARMACOLOGY, Pharmacokinetics).

Serotonin syndrome may include mental-status changes (e.g., agitation, hallucinations, coma), autonomic instability (e.g., tachycardia, labile blood pressure, hyperthermia), neuromuscular aberrations (e.g., hyperreflexia, incoordination), and/or gastrointestinal symptoms (e.g., nausea, vomiting, diarrhea).

Hypersensitivity/Anaphylaxis

Serious and rarely fatal anaphylactic reactions have been reported in patients receiving therapy with tramadol. When these events do occur it is often following the first dose. Other reported allergic reactions include pruritus, hives, bronchospasm, angioedema, toxic epidermal necrolysis, and Stevens-Johnson syndrome. Patients with a history of anaphylactoid reactions to codeine and other opioids may be at increased risk and therefore should not receive ULTRACET® (see CONTRAINDICATIONS).

There have been post-marketing reports of hypersensitivity and anaphylaxis associated with the use of acetaminophen. Clinical signs included swelling of the face, mouth, and throat, respiratory distress, urticaria, rash, pruritus, and vomiting. There were infrequent reports of life-threatening anaphylaxis requiring emergency medical attention. Instruct patients to discontinue ULTRACET® immediately and seek medical care if they experience these symptoms. Do not prescribe ULTRACET® for patients with acetaminophen allergy.

Respiratory Depression

Administer ULTRACET® cautiously in patients at risk for respiratory depression. In these patients, alternative non-opioid analgesics should be considered. When large doses of tramadol are administered with anesthetic medications or alcohol, respiratory depression may result. Respiratory depression should be treated as an overdose. If naloxone is to be administered, use cautiously because it may precipitate seizures (see WARNINGS, Seizure Risk and OVERDOSAGE).

Interaction With Central Nervous System (CNS) Depressants

ULTRACET® should be used with caution and in reduced dosages when administered to patients receiving CNS depressants such as alcohol, opioids, anesthetic agents, narcotics, phenothiazines, tranquilizers, or sedative hypnotics. Tramadol increases the risk of CNS and respiratory depression in these patients.

Interactions With Alcohol and Drugs of Abuse

Tramadol may be expected to have additive effects when used in conjunction with alcohol, other opioids, or illicit drugs that cause central nervous system depression.

Increased Intracranial Pressure or Head Trauma

ULTRACET® should be used with caution in patients with increased intracranial pressure or head injury. The respiratory depressant effects of opioids include carbon dioxide retention and secondary elevation of cerebrospinal fluid pressure and may be markedly exaggerated in these patients. Additionally, pupillary changes (miosis) from tramadol may obscure the existence, extent, or course of intracranial pathology. Clinicians should also maintain a high index of suspicion for adverse drug reactions when evaluating altered mental status in these patients if they are receiving ULTRACET® (see WARNINGS, Respiratory Depression).

Use in Ambulatory Patients

Tramadol may impair the mental and or physical abilities required for the performance of potentially hazardous tasks such as driving a car or operating machinery. The patient using this drug should be cautioned accordingly.

Use With MAO Inhibitors and Serotonin Re-uptake Inhibitors

Use ULTRACET® with great caution in patients taking monoamine oxidase inhibitors. Animal studies have shown increased deaths with combined administration of MAO inhibitors and tramadol. Concomitant use of tramadol with MAO inhibitors or SSRIs increases the risk of adverse events, including seizure and serotonin syndrome.

Use With Alcohol

ULTRACET® should not be used concomitantly with alcohol consumption. The use of ULTRACET® in patients with liver disease is not recommended.

Use With Other Acetaminophen-containing Products

Due to the potential for acetaminophen hepatotoxicity at doses higher than the recommended dose, ULTRACET® should not be used concomitantly with other acetaminophen-containing products.

Misuse, Abuse and Diversion

Tramadol has mu-opioid agonist activity. ULTRACET®, a tramadol-containing product, can be sought by drug abusers and people with addiction disorders and may be subject to criminal diversion. The possibility of illegal or illicit use should be considered when prescribing or dispensing ULTRACET® in situations where the physician or pharmacist is concerned about an increased risk of misuse, abuse, or diversion. Misuse or abuse poses a significant risk to the abuser that could result in overdose and death (see DRUG ABUSE AND DEPENDENCE and OVERDOSAGE).

Concerns about abuse, addiction, and diversion should not prevent the proper management of pain. The development of addiction to opioid analgesics in properly managed patients with pain has been reported to be rare. However, data are not available to establish the true incidence of addiction in chronic pain patients.

Risk of Overdosage

Patients taking tramadol should be warned not to exceed the dose recommended by their physician. Tramadol products in excessive doses, either alone or in combination with other CNS depressants, including alcohol, are a cause of drug-related deaths. Patients should be cautioned about the concomitant use of tramadol products and alcohol because of potentially serious CNS additive effects of these agents. Because of its added depressant effects, tramadol should be prescribed with caution for those patients whose medical condition requires the concomitant administration of sedatives, tranquilizers, muscle relaxants, tricyclic antidepressants, or other CNS depressant drugs. Patients should be advised of the additive depressant effects of these combinations.

Serious potential consequences of overdosage with tramadol are central nervous system depression, respiratory depression, and death. Some deaths have occurred as a consequence of the accidental ingestion of excessive quantities of tramadol alone or in combination with other drugs. In treating an overdose, primary attention should be given to maintaining adequate ventilation along with general supportive treatment (see OVERDOSAGE).

A serious potential consequence of overdosage with acetaminophen is hepatic (centrilobular) necrosis, leading to hepatic failure and death. Emergency help should be sought immediately and treatment initiated immediately if overdose is suspected, even if symptoms are not apparent.

Withdrawal

Withdrawal symptoms may occur if ULTRACET® is discontinued abruptly (see also DRUG ABUSE AND DEPENDENCE). Reported symptoms have included anxiety, sweating, insomnia, rigors, pain, nausea, tremors, diarrhea, upper respiratory symptoms, piloerection, and rarely hallucinations. Other symptoms that have been reported less frequently with ULTRACET® discontinuation include: panic attacks, severe anxiety, and paresthesias. Clinical experience suggests that withdrawal symptoms may be avoided by tapering ULTRACET® at the time of discontinuation.

PRECAUTIONS

General

The recommended dose of ULTRACET® should not be exceeded.

Do not co-administer ULTRACET® with other tramadol or acetaminophen-containing products (see WARNINGS, Use With Other Acetaminophen-containing Products and Risk of Overdosage).

Pediatric Use

The safety and effectiveness of ULTRACET® has not been studied in the pediatric population.

Geriatric Use

In general, dose selection for an elderly patient should be cautious, reflecting the greater frequency of decreased hepatic, renal, or cardiac function; of concomitant disease; and multiple drug therapy.

Acute Abdominal Conditions

The administration of ULTRACET® may complicate the clinical assessment of patients with acute abdominal conditions.

Use in Renal Disease

ULTRACET® has not been studied in patients with impaired renal function. Experience with tramadol suggests that impaired renal function results in a decreased rate and extent of excretion of tramadol and its active metabolite, M1. In patients with creatinine clearances of less than 30 mL/min, it is recommended that the dosing interval of ULTRACET® be increased, not to exceed 2 tablets every 12 hours.

Use in Hepatic Disease

ULTRACET® has not been studied in patients with impaired hepatic function. The use of ULTRACET® in patients with hepatic impairment is not recommended (see WARNINGS, Use With Alcohol).

Information for Patients

- Do not take ULTRACET® if you are allergic to any of its ingredients.
- If you develop signs of allergy such as a rash or difficulty breathing, stop taking ULTRACET® and contact your healthcare provider immediately.
- Do not take more than 4,000 milligrams of acetaminophen per day. Call your doctor if you took more than the recommended dose.
- Do not take ULTRACET® in combination with other tramadol or acetaminophen-containing products, including over-the-counter preparations.
- ULTRACET® may cause seizures and/or serotonin syndrome with concomitant use of serotonergic agents (including SSRIs, SNRIs, and triptans) or drugs that significantly reduce the metabolic clearance of tramadol.
- ULTRACET® may impair mental or physical abilities required for the performance of potentially hazardous tasks such as driving a car or operating machinery.
- ULTRACET® should not be taken concomitantly with alcohol-containing beverages during the course of treatment with ULTRACET®.
- ULTRACET® should be used with caution when taking medications such as tranquilizers, hypnotics, or other opiate-containing analgesics.
- Inform the physician if you are pregnant, think you might become pregnant, or are trying to become pregnant (see PRECAUTIONS, Labor and Delivery).
- Understand the single-dose and 24-hour dose limit and the time interval between doses, since exceeding these recommendations can result in respiratory depression, seizures, hepatic toxicity, and death.

Drug Interactions

CYP2D6 and CYP3A4 Inhibitors

Concomitant administration of CYP2D6 and/or CYP3A4 inhibitors (see CLINICAL PHARMACOLOGY, Pharmacokinetics), such as quinidine, fluoxetine, paroxetine. and amitriptyline (CYP2D6 inhibitors), and ketoconazole and erythromycin (CYP3A4 inhibitors), may reduce metabolic clearance of tramadol, increasing the risk for serious adverse events including seizures and serotonin syndrome.

Serotonergic Drugs

There have been postmarketing reports of serotonin syndrome with use of tramadol and SSRIs/SNRIs or MAOIs and α2-adrenergic blockers. Caution is advised when ULTRACET® is coadministered with other drugs that may affect the serotonergic neurotransmitter systems, such as SSRIs, MAOIs, triptans, linezolid (an antibiotic which is a reversible non-selective MAOI), lithium, or St. John's Wort. If concomitant treatment of ULTRACET® with a drug affecting the serotonergic neurotransmitter system is clinically warranted, careful observation of the patient is advised, particularly during treatment initiation and dose increases (see WARNINGS, Serotonin Syndrome).

Triptans

Based on the mechanism of action of tramadol and the potential for serotonin syndrome, caution is advised when ULTRACET® is coadministered with a triptan. If concomitant treatment of ULTRACET® with a triptan is clinically warranted, careful observation of the patient is advised, particularly during treatment initiation and dose increases (see WARNINGS, Serotonin Syndrome).

Use With Carbamazepine

Patients taking carbamazepine may have a significantly reduced analgesic effect of tramadol. Because carbamazepine increases tramadol metabolism and because of the seizure risk associated with tramadol, concomitant administration of ULTRACET® and carbamazepine is not recommended.

Use With Quinidine

Tramadol is metabolized to M1 by CYP2D6. Quinidine is a selective inhibitor of that isoenzyme; so that concomitant administration of quinidine and tramadol results in increased concentrations of tramadol and reduced concentrations of M1. The clinical consequences of these findings are unknown. In vitro drug interaction studies in human liver microsomes indicate that tramadol has no effect on quinidine metabolism.

Potential for Other Drugs to Affect Tramadol

In vitro drug interaction studies in human liver microsomes indicate that concomitant administration with inhibitors of CYP2D6 such as fluoxetine, paroxetine, and amitriptyline could result in some inhibition of the metabolism of tramadol. Administration of CYP3A4 inhibitors, such as ketoconazole and erythromycin, or inducers, such as rifampin and St. John's Wort, with ULTRACET® may affect the metabolism of tramadol, leading to altered tramadol exposure.

Potential for Tramadol to Affect Other Drugs

In vitro studies indicate that tramadol is unlikely to inhibit the CYP3A4-mediated metabolism of other drugs when tramadol is administered concomitantly at therapeutic doses. Tramadol does not appear to induce its own metabolism in humans, since observed maximal plasma concentrations after multiple oral doses are higher than expected based on single-dose data. Tramadol is a mild inducer of selected drug metabolism pathways measured in animals.

Use With Cimetidine

Concomitant administration of ULTRACET® and cimetidine has not been studied. Concomitant administration of tramadol and cimetidine does not result in clinically significant changes in tramadol pharmacokinetics. Therefore, no alteration of the ULTRACET® dosage regimen is recommended.

Use With Digoxin

Post-marketing surveillance of tramadol has revealed rare reports of digoxin toxicity.

Use With Warfarin-Like Compounds

Post-marketing surveillance of both tramadol and acetaminophen individual products have revealed rare alterations of warfarin effect, including elevation of prothrombin times.

While such changes have been generally of limited clinical significance for the individual products, periodic evaluation of prothrombin time should be performed when ULTRACET® and warfarin-like compounds are administered concurrently.

Carcinogenesis, Mutagenesis, Impairment of Fertility

There are no animal or laboratory studies on the combination product (tramadol and acetaminophen) to evaluate carcinogenesis, mutagenesis, or impairment of fertility.

A slight but statistically significant increase in two common murine tumors, pulmonary and hepatic, was observed in a mouse carcinogenicity study, particularly in aged mice. Mice were dosed orally up to 30 mg/kg (90 mg/m^2 or 0.5 times the maximum daily human tramadol dosage of 185 mg/m^2) for approximately two years, although the study was not done with the Maximum Tolerated Dose. This finding is not believed to suggest risk in humans. No such finding occurred in a rat carcinogenicity study (dosing orally up to 30 mg/kg, 180 mg/m^2, or 1 time the maximum daily human tramadol dosage).

Tramadol was not mutagenic in the following assays: Ames Salmonella microsomal activation test, CHO/HPRT mammalian cell assay, mouse lymphoma assay (in the absence of metabolic activation), dominant lethal mutation tests in mice, chromosome aberration test in Chinese hamsters, and bone marrow micronucleus tests in mice and Chinese hamsters. Weakly mutagenic results occurred in the presence of metabolic activation in the mouse lymphoma assay and micronucleus test in rats. Overall, the weight of evidence from these tests indicates that tramadol does not pose a genotoxic risk to humans.

No effects on fertility were observed for tramadol at oral dose levels up to 50 mg/kg (350 mg/m^2) in male rats and 75 mg/kg (450 mg/m^2) in female rats. These dosages are 1.6 and 2.4 times the maximum daily human tramadol dosage of 185 mg/m^2.

Pregnancy

Teratogenic Effects

Pregnancy Category C

No drug-related teratogenic effects were observed in the progeny of rats treated orally with tramadol and acetaminophen. The tramadol/acetaminophen combination product was shown to be embryotoxic and fetotoxic in rats at a maternally toxic dose, 50/434 mg/kg tramadol/acetaminophen (300/2604 mg/m^2 or 1.6 times the maximum daily human tramadol/acetaminophen dosage of 185/1591 mg/m^2), but was not teratogenic at this dose level. Embryo and fetal toxicity consisted of decreased fetal weights and increased supernumerary ribs.

Non-teratogenic Effects

Tramadol alone was evaluated in peri- and post-natal studies in rats. Progeny of dams receiving oral (gavage) dose levels of 50 mg/kg (300 mg/m^2 or 1.6 times the maximum daily human tramadol dosage) or greater had decreased weights, and pup survival was decreased early in lactation at 80 mg/kg (480 mg/m^2 or 2.6 times the maximum daily human tramadol dosage).

There are no adequate and well-controlled studies in pregnant women. ULTRACET® should be used during pregnancy only if the potential benefit justifies the potential risk to the fetus. Neonatal seizures, neonatal withdrawal syndrome, fetal death and stillbirth have been reported with tramadol hydrochloride during post-marketing.

Labor and Delivery

ULTRACET® should not be used in pregnant women prior to or during labor unless the potential benefits outweigh the risks. Safe use in pregnancy has not been established. Chronic use during pregnancy may lead to physical dependence and post-partum withdrawal symptoms in the newborn (see DRUG ABUSE AND DEPENDENCE). Tramadol has been shown to cross the placenta. The mean ratio of serum tramadol in the umbilical veins compared to maternal veins was 0.83 for 40 women given tramadol during labor.

The effect of ULTRACET®, if any, on the later growth, development, and functional maturation of the child is unknown.

Nursing Mothers

ULTRACET® is not recommended for obstetrical preoperative medication or for post-delivery analgesia in nursing mothers because its safety in infants and newborns has not been studied.

Following a single IV 100 mg dose of tramadol, the cumulative excretion in breast milk within 16 hours post-dose was 100 µg of tramadol (0.1% of the maternal dose) and 27 µg of M1.

ADVERSE REACTIONS

Table 2 reports the incidence rate of treatment-emergent adverse events over five days of ULTRACET® use in clinical trials (subjects took an average of at least 6 tablets per day).

Table 2: Incidence of Treatment-Emergent Adverse Events (≥2.0%)
Body System Preferred Term | ULTRACET® (N=142) (%)
Gastrointestinal System Disorders
Constipation | 6
Diarrhea | 3
Nausea | 3
Dry Mouth | 2
Psychiatric Disorders
Somnolence | 6
Anorexia | 3
Insomnia | 2
Central & Peripheral Nervous System
Dizziness | 3
Skin and Appendages
Sweating Increased | 4
Pruritus | 2
Reproductive Disorders, Male [Number of males = 62]
Prostatic Disorder | 2

Incidence at least 1%, causal relationship at least possible or greater: the following lists adverse reactions that occurred with an incidence of at least 1% in single-dose or repeated-dose clinical trials of ULTRACET®.

Body as a Whole – Asthenia, fatigue, hot flushes

Central and Peripheral Nervous System – Dizziness, headache, tremor

Gastrointestinal System – Abdominal pain, constipation, diarrhea, dyspepsia, flatulence, dry mouth, nausea, vomiting

Psychiatric Disorders – Anorexia, anxiety, confusion, euphoria, insomnia, nervousness, somnolence

Skin and Appendages – Pruritus, rash, increased sweating

Selected Adverse events occurring at less than 1%: the following lists clinically relevant adverse reactions that occurred with an incidence of less than 1% in ULTRACET® clinical trials.

Body as a Whole – Chest pain, rigors, syncope, withdrawal syndrome

Cardiovascular Disorders – Hypertension, aggravated hypertension, hypotension

Central and Peripheral Nervous System – Ataxia, convulsions, hypertonia, migraine, aggravated migraine, involuntary muscle contractions, paresthesias, stupor, vertigo

Gastrointestinal System – Dysphagia, melena, tongue edema

Hearing and Vestibular Disorders – Tinnitus

Heart Rate and Rhythm Disorders – Arrhythmia, palpitation, tachycardia

Liver and Biliary System – Hepatic function abnormal

Metabolic and Nutritional Disorders – Weight decrease

Psychiatric Disorders – Amnesia, depersonalization, depression, drug abuse, emotional lability, hallucination, impotence, paroniria, abnormal thinking

Red Blood Cell Disorders – Anemia

Respiratory System – Dyspnea

Urinary System – Albuminuria, micturition disorder, oliguria, urinary retention

Vision Disorders – Abnormal vision

Other clinically significant adverse experiences previously reported with tramadol hydrochloride

Other events which have been reported with the use of tramadol products and for which a causal association has not been determined include: vasodilation, orthostatic hypotension, myocardial ischemia, pulmonary edema, allergic reactions (including anaphylaxis and urticaria, Stevens-Johnson syndrome/TENS), cognitive dysfunction, difficulty concentrating, depression, suicidal tendency, hepatitis, liver failure, and gastrointestinal bleeding. Reported laboratory abnormalities included elevated creatinine and liver function tests. Serotonin syndrome (whose symptoms may include mental status change, hyperreflexia, fever, shivering, tremor, agitation, diaphoresis, seizures, and coma) has been reported with tramadol when used concomitantly with other serotonergic agents such as SSRIs and MAOIs.

Other clinically significant adverse experiences previously reported with acetaminophen

Allergic reactions (primarily skin rash) or reports of hypersensitivity secondary to acetaminophen are rare and generally controlled by discontinuation of the drug and, when necessary, symptomatic treatment.

DRUG ABUSE AND DEPENDENCE

Abuse

Tramadol has mu-opioid agonist activity. ULTRACET®, a tramadol-containing product, can be abused and may be subject to criminal diversion.

Addiction is a primary, chronic, neurobiologic disease, with genetic, psychosocial, and environmental factors influencing its development and manifestations. Drug addiction is characterized by behaviors that include one or more of the following: impaired control over drug use, compulsive use, use for non-medical purposes, continued use despite harm or risk of harm, and craving. Drug addiction is a treatable disease, utilizing a multidisciplinary approach, but relapse is common.

"Drug-seeking" behavior is very common in addicts and drug abusers. Drug-seeking tactics include emergency calls or visits near the end of office hours, refusal to undergo appropriate examination, testing or referral, repeated "loss" of prescriptions, tampering with prescriptions, and reluctance to provide prior medical records or contact information for other treating physician(s). "Doctor shopping" to obtain additional prescriptions is common among drug abusers and people suffering from untreated addiction.

Abuse and addiction are separate and distinct from physical dependence and tolerance. Physicians should be aware that addiction may not be accompanied by concurrent tolerance and symptoms of physical dependence in all addicts. In addition, abuse of ULTRACET® can occur in the absence of true addiction and is characterized by misuse for non-medical purposes, often in combination with other psychoactive substances.

Concerns about abuse and addiction should not prevent the proper management of pain. However, all patients treated with opioids require careful monitoring for signs of abuse and addiction, because use of opioid analgesic products carries the risk of addiction even under appropriate medical use.

Proper assessment of the patient and periodic re-evaluation of therapy are appropriate measures that help to limit the potential abuse of this product.

ULTRACET® is intended for oral use only.

Dependence

Tolerance is the need for increasing doses of drugs to maintain a defined effect such as analgesia (in the absence of disease progression or other external factors). Physical dependence is manifested by withdrawal symptoms after abrupt discontinuation of a drug or upon administration of an antagonist (see also WARNINGS, Withdrawal).

The opioid abstinence or withdrawal syndrome is characterized by some or all of the following: restlessness, lacrimation, rhinorrhea, yawning, perspiration, chills, myalgia, and mydriasis. Other symptoms also may develop, including irritability, anxiety, backache, joint pain, weakness, abdominal cramps, insomnia, nausea, anorexia, vomiting, diarrhea, or increased blood pressure, respiratory rate, or heart rate.

Generally, tolerance and/or withdrawal are more likely to occur the longer a patient is on continuous therapy with ULTRACET®.

OVERDOSAGE

ULTRACET® is a combination product. The clinical presentation of overdose may include the signs and symptoms of tramadol toxicity, acetaminophen toxicity or both. The initial symptoms of tramadol overdosage may include respiratory depression and/or seizures. The initial symptoms seen within the first 24 hours following an acetaminophen overdose are: anorexia, nausea, vomiting, malaise, pallor and diaphoresis. An overdosage of ULTRACET® may be a potentially lethal polydrug overdose, and consultation with a regional poison control center is recommended.

Tramadol

Acute overdosage with tramadol can be manifested by respiratory depression, somnolence progressing to stupor or coma, skeletal muscle flaccidity, cold and clammy skin, constricted pupils, seizures, bradycardia, hypotension, cardiac arrest, and death.

Deaths due to overdose have been reported with abuse and misuse of tramadol (see WARNINGS, Misuse, Abuse, and Diversion). Review of case reports has indicated that the risk of fatal overdose is further increased when tramadol is abused concurrently with alcohol or other CNS depressants, including other opioids.

In the treatment of tramadol overdosage, primary attention should be given to the re-establishment of a patent airway and institution of assisted or controlled ventilation. Supportive measures (including oxygen and vasopressors) should be employed in the management of circulatory shock and pulmonary edema accompanying overdose as indicated. Cardiac arrest or arrhythmias may require cardiac massage or defibrillation.

While naloxone will reverse some, but not all, symptoms caused by overdosage with tramadol, the risk of seizures is also increased with naloxone administration. In animals, convulsions following the administration of toxic doses of ULTRACET® could be suppressed with barbiturates or benzodiazepines but were increased with naloxone. Naloxone administration did not change the lethality of an overdose in mice. Hemodialysis is not expected to be helpful in an overdose because it removes less than 7% of the administered dose in a 4-hour dialysis period.

Acetaminophen

In acetaminophen overdosage, dose-dependent, potentially fatal hepatic necrosis is the most serious adverse effect. Renal tubular necrosis, hypoglycemic coma, and coagulation defects also may occur. Early symptoms following a potentially hepatotoxic overdose may include: nausea, vomiting, diaphoresis, and general malaise. Clinical and laboratory evidence of hepatic toxicity may not be apparent until 48 to 72 hours post-ingestion.

In the treatment of acetaminophen overdosage, gastric decontamination with activated charcoal should be administered just prior to N-acetylcysteine (NAC) to decrease systemic absorption if acetaminophen ingestion is known or suspected to have occurred within a few hours of presentation. Serum acetaminophen levels should be obtained immediately if the patient presents 4 or more hours after ingestion to assess potential risk of hepatotoxicity; acetaminophen levels drawn less than 4 hours post-ingestion may be misleading. To obtain the best possible outcome, NAC should be administered as soon as possible where impending or evolving liver injury is suspected. Intravenous NAC may be administered when circumstances preclude oral administration.

Vigorous supportive therapy is required in severe intoxication. Procedures to limit the continuing absorption of the drug must be readily performed since the hepatic injury is dose-dependent and occurs early in the course of intoxication.

DOSAGE AND ADMINISTRATION

For the short-term (five days or less) management of acute pain, the recommended dose of ULTRACET® is 2 tablets every 4 to 6 hours as needed for pain relief, up to a maximum of 8 tablets per day.

Individualization of Dose

In patients with creatinine clearances of less than 30 mL/min, it is recommended that the dosing interval of ULTRACET® be increased not to exceed 2 tablets every 12 hours. Dose selection for an elderly patient should be cautious, in view of the potential for greater sensitivity to adverse events.

HOW SUPPLIED

ULTRACET® (tramadol hydrochloride/acetaminophen) Tablets with tramadol 37.5 mg and acetaminophen 325 mg are light yellow, coated, capsule-shaped tablets imprinted "O-M" on one side and "650" on the other and are available as follows:

NDC 54868-4703-1 | Bottles of 10 tablets
NDC 54868-4703-4 | Bottles of 60 tablets

STORAGE AND HANDLING

Dispense in a tight container. Store at 25°C (77°F); excursions permitted to 15 – 30°C (59 – 86°F).

Manufactured by:
Janssen Ortho, LLC
Gurabo, Puerto Rico 00778

Manufactured for:

PriCara, Division of Ortho-McNeil-Janssen Pharmaceuticals, Inc.
Raritan, New Jersey 08869

© Ortho-McNeil-Janssen Pharmaceuticals, Inc. 2003

Revised June 2011

Relabeling and Repackaging by:
Physicians Total Care, Inc.
Tulsa, Oklahoma 74146

PRINCIPAL DISPLAY PANEL

ULTRACET®
(37.5 mg tramadol
HCl/325 mg
acetaminophen
tablets)

Rx only.